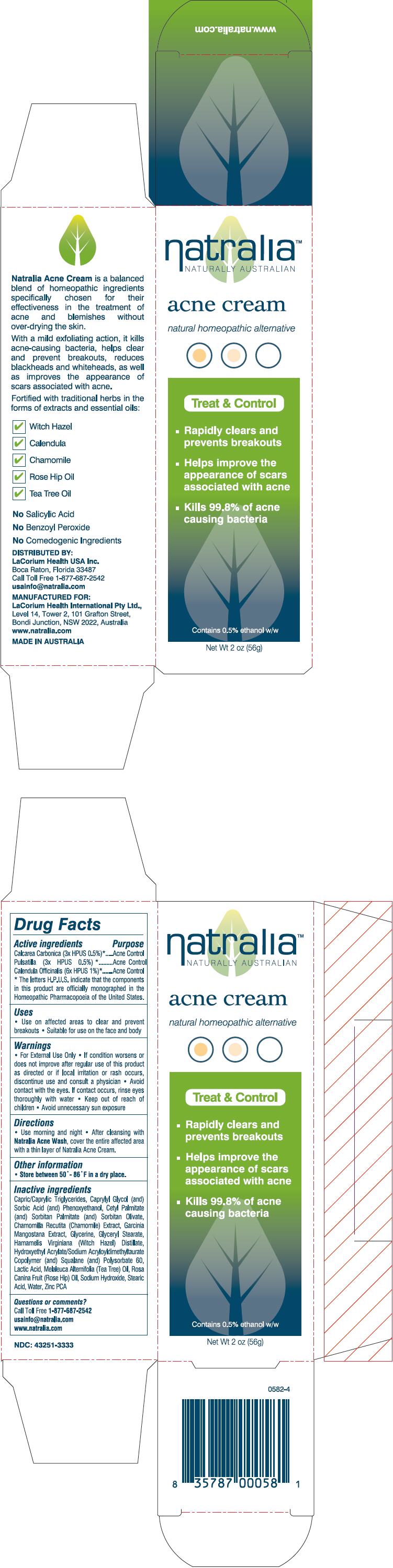 DRUG LABEL: Natralia 
NDC: 43251-3333 | Form: CREAM
Manufacturer: LaCorium Health International Pty Ltd
Category: homeopathic | Type: HUMAN OTC DRUG LABEL
Date: 20121219

ACTIVE INGREDIENTS: CALENDULA OFFICINALIS FLOWER 6 [hp_X]/1 g; CALCIUM CARBONATE 3 [hp_X]/1 g; PULSATILLA VULGARIS 3 [hp_X]/1 g
INACTIVE INGREDIENTS: Chamomile; Glycerin; Glyceryl Monostearate; Lactic Acid; Zinc Pidolate; Cetyl Palmitate; Sorbitan Monopalmitate; Sorbitan Olivate; Caprylyl Glycol; Sorbic Acid; Phenoxyethanol; Squalane; Polysorbate 60; Stearic Acid; Rosa Canina Fruit Oil; Tea Tree Oil; Witch Hazel

natralia™
NATURALLY AUSTRALIAN
acne cream

Drug Facts

ACTIVE INGREDIENT

Active ingredients | Purpose
Calcarea Carbonica (3× HPUS 0.5%) [The letters H.P.U.S. indicate that the components in this product are officially monographed in the Homeopathic Pharmacopoeia of the United States.] | Acne Control
Pulsatilla Vulgaris (3× HPUS 0.5%) | Acne Control
Calendula Officinalis (6× HPUS 1%) | Acne Control

Uses

- Use on affected areas to clear and prevent breakouts.
- Suitable for use on the face and body

Warnings

- For External Use Only

STOP USE

- If condition worsens or does not improve after regular use of this product as directed or if local irritation or rash occurs, discontinue use and consult a physician

WHEN USING

- Avoid contact with the eyes. If contact occurs, rinse eyes thoroughly with water

- Keep out of reach of children

WHEN USING

- Avoid unnecessary sun exposure

Directions

- Use morning and night
- After cleansing with Natralia Acne Wash, cover the entire affected area with a thin layer of Natralia Acne Cream.

Other information

- Store between 50°- 86°F in a dry place.

Inactive ingredients

Capric/Caprylic Triglycerides, Caprylyl Glycol (and) Sorbic Acid (and) Phenoxyethanol, Cetyl Palmitate (and) Sorbitan Palmitate (and) Sorbitan Olivate, Chamomilla Recutita (Chamomile) Extract, Garcinia Mangostana Extract, Glycerine, Glyceryl Stearate, Hamamelis Virginiana (Witch Hazel) Distillate, Hydroxyethyl Acrylate/Sodium Acryloyldimethyltaurate Copolymer (and) Squalane (and) Polysorbate 60, Lactic Acid, Melaleuca Alternifolia (Tea Tree) Oil, Rosa Canina Fruit (Rose Hip) Oil, Sodium Hydroxide, Stearic Acid, Water, Zinc PCA

Questions or comments?

Call Toll Free 1-877-687-2542

usainfo@natralia.com.au

www.natralia.com.au/usa

PRINCIPAL DISPLAY PANEL - 56g Bottle Carton

natralia™
NATURALLY AUSTRALIAN

acne cream

natural homeopathic alternative

Treat & Control

- Rapidly clears and
  prevents breakouts
- Helps improve the
  appearance of scars
  associated with acne
- Kills 99.8% of acne
  causing bacteria

Contains 0.5% ethanol w/w

Net Wt 2 oz (56g)